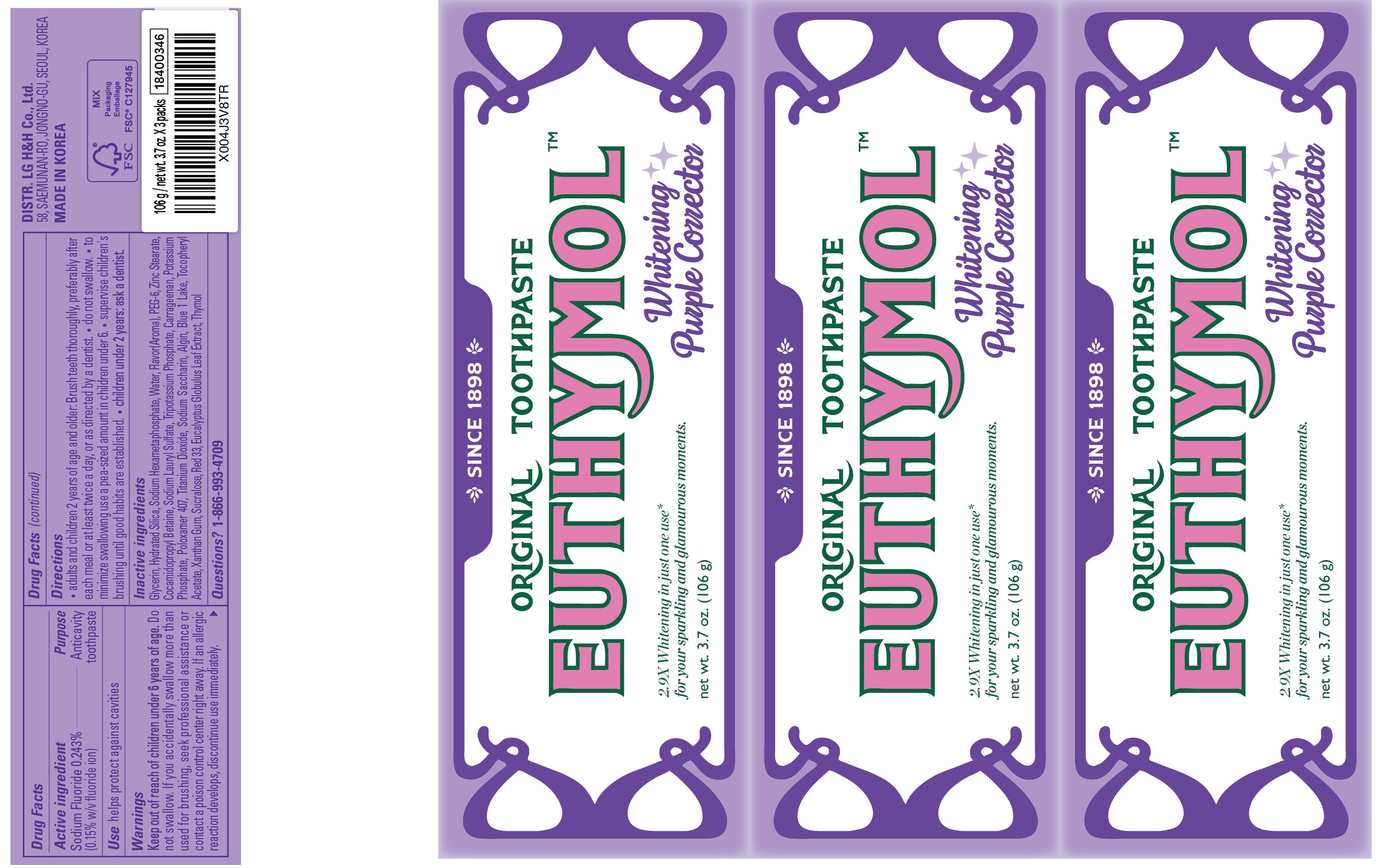 DRUG LABEL: Euthymol Whitening Purple Corrector
NDC: 53208-563 | Form: PASTE, DENTIFRICE
Manufacturer: LG HOUSEHOLD & HEALTH CARE LTD.
Category: otc | Type: HUMAN OTC DRUG LABEL
Date: 20250903

ACTIVE INGREDIENTS: SODIUM FLUORIDE 1.5 mg/1 g
INACTIVE INGREDIENTS: BLUE 1 LAKE; SODIUM HEXAMETAPHOSPHATE; TITANIUM DIOXIDE; EUCALYPTUS GLOBULUS LEAF; GLYCERIN; SODIUM LAURYL SULFATE; RED 33; POTASSIUM PHOSPHATE, TRIBASIC; SUCRALOSE; ALPHA-TOCOPHEROL ACETATE; XANTHAN GUM; THYMOL; HYDRATED SILICA; COCAMIDOPROPYL BETAINE; SODIUM SACCHARIN; CARRAGEENAN; POTASSIUM PHOSPHATE; POLOXAMER 407; ZINC STEARATE; PEG-6; WATER; ALGIN

Euthymol Whitening Purple Corrector Toothpaste 106G X 3 Cello Pack Banding

Active ingredient

Sodium Fluoride 0.243%

(0.15% w/v fluoride ion)

Purpose

Anticavity toothpaste

Use

helps protect against cavities

WARNINGS

Keep out of reach of children under 6 years of age.

Do not

Do not swallow. If you accidentally swallow more than used for brushing, seek professional assistance or contact a poison control center right away. If an allergic reaction develops, discontinue use immediately.

Directions

- adults and children 2 years of age and older. Brush teeth thoroughly, preferably after each meal or at least twice a day, or as directed by a dentist.
- do not swallow.
- to minimize swallowing use a pea-sized amount in children under 6.
- supervise children's brushing until good habits are established.
- children under 2 years: ask a dentist.

Inactive ingredients

GLYCERIN, HYDRATED SILICA, SODIUM HEXAMETAPHOSPHATE, WATER, FLAVOR(AROMA), PEG-6, ZINC STEARATE, COCAMIDOPROPYL BETAINE, SODIUM LAURYL SULFATE, TRIPOTASSIUM PHOSPHATE, CARRAGEENAN, POTASSIUM PHOSPHATE, POLOXAMER 407, TITANIUM DIOXIDE, SODIUM SACCHARIN, ALGIN, BLUE 1 LAKE, TOCOPHERYL ACETATE, XANTHAN GUM, SUCRALOSE, RED 33, EUCALYPTUS GLOBULUS LEAF EXTRACT, THYMOL

Questions?

1-866-993-4709